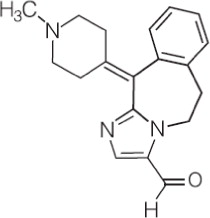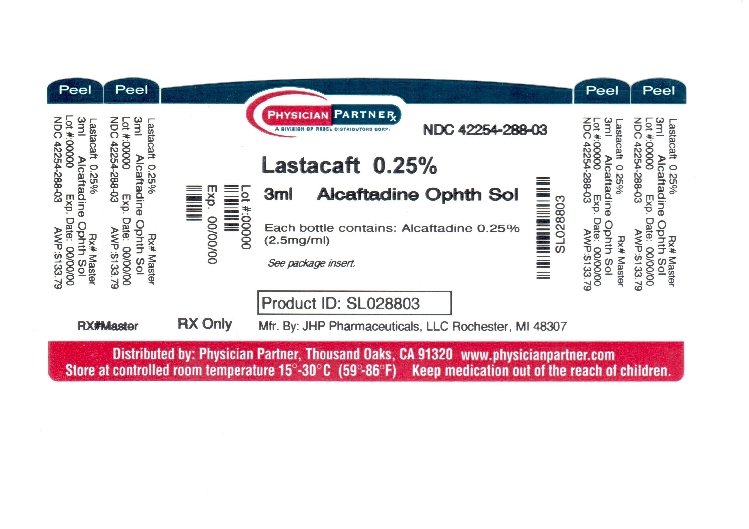 DRUG LABEL: LASTACAFT
NDC: 42254-288 | Form: SOLUTION/ DROPS
Manufacturer: Rebel Distributors Corp
Category: prescription | Type: HUMAN PRESCRIPTION DRUG LABEL
Date: 20120905

ACTIVE INGREDIENTS: alcaftadine 2.5 mg/1 mL
INACTIVE INGREDIENTS: benzalkonium chloride; edetate disodium; sodium phosphate, monobasic; water; sodium chloride; sodium hydroxide; hydrochloric acid

HIGHLIGHTS OF PRESCRIBING INFORMATION

These highlights do not include all the information needed to use LASTACAFT® safely and effectively. See full prescribing information for LASTACAFT®.
LASTACAFT® (alcaftadine ophthalmic solution) 0.25%
Initial U.S. Approval: 2010

1 INDICATIONS AND USAGE

LASTACAFT® is an H1 histamine receptor antagonist indicated for the prevention of itching associated with allergic conjunctivitis. (1)

2 DOSAGE AND ADMINISTRATION

Instill one drop in each eye once daily. (2)

3 DOSAGE FORMS AND STRENGTHS

Ophthalmic solution containing alcaftadine, 0.25% (2.5 mg/mL) (3)

5 WARNINGS AND PRECAUTIONS

- To minimize the risk of contamination, do not touch dropper tip to any surface. Keep bottle tightly closed when not in use. (5.1)
- LASTACAFT® should not be used to treat contact lens-related irritation. (5.2)
- Remove contact lenses prior to instillation of LASTACAFT®. (5.2)

6 ADVERSE REACTIONS

The most common ocular adverse reactions, occurring in < 4% of LASTACAFT® treated eyes, were eye irritation, burning and/or stinging on instillation, eye redness, and eye pruritus. (6.1)

The most common non-ocular adverse reactions, occurring in < 3% of subjects with LASTACAFT® treated eyes, were nasopharyngitis, headache and influenza. (6.2)

To report SUSPECTED ADVERSE REACTIONS, contact Allergan at 1-800-433-8871 or FDA at 1-800-FDA-1088 or www.fda.gov/medwatch.

FULL PRESCRIBING INFORMATION

1 INDICATIONS AND USAGE

LASTACAFT® is an H1 histamine receptor antagonist indicated for the prevention of itching associated with allergic conjunctivitis.

2 DOSAGE AND ADMINISTRATION

Instill one drop in each eye once daily.

3 DOSAGE FORMS AND STRENGTHS

Topical ophthalmic solution containing alcaftadine, 0.25% (2.5 mg/mL).

4 CONTRAINDICATIONS

None.

5 WARNINGS AND PRECAUTIONS

5.1 Contamination of Tip and Solution

To minimize contaminating the dropper tip and solution, care should be taken not to touch the eyelids or surrounding areas with the dropper tip of the bottle. Keep bottle tightly closed when not in use.

5.2 Contact Lens Use

Patients should be advised not to wear a contact lens if their eye is red. LASTACAFT® should not be used to treat contact lens-related irritation.

LASTACAFT® should not be instilled while wearing contact lenses. Remove contact lenses prior to instillation of LASTACAFT®. The preservative in LASTACAFT®, benzalkonium chloride, may be absorbed by soft contact lenses. Lenses may be reinserted after 10 minutes following administration of LASTACAFT®.

5.3 Topical Ophthalmic Use Only

LASTACAFT® is for topical ophthalmic use only.

6 ADVERSE REACTIONS

Because clinical trials are conducted under widely varying conditions, adverse reaction rates observed in the clinical trials of a drug cannot be directly compared to rates in the clinical trials of another drug and may not reflect the rates observed in clinical practice.

6.1 Ocular Adverse Reactions

The most frequent ocular adverse reactions, occurring in < 4% of LASTACAFT® treated eyes, were eye irritation, burning and/or stinging upon instillation, eye redness and eye pruritus.

6.2 Non-ocular Adverse Reactions

The most frequent non-ocular adverse reactions, occurring in < 3% of subjects with LASTACAFT® treated eyes, were nasopharyngitis, headache and influenza. Some of these events were similar to the underlying disease being studied.

8 USE IN SPECIFIC POPULATIONS

8.1 Pregnancy

Pregnancy Category B. Reproduction studies performed in rats and rabbits revealed no evidence of impaired female reproduction or harm to the fetus due to alcaftadine. Oral doses in rats and rabbits of 20 and 80 mg/kg/day, respectively, produced plasma exposure levels approximately 200 and 9000 times the plasma exposure at the recommended human ocular dose. There are however, no adequate and well controlled studies in pregnant women. Because animal reproduction studies are not always predictive of human response, this drug should be used during pregnancy only if clearly needed.

8.3 Nursing Mothers

It is not known whether this drug is excreted in human milk. Because many drugs are excreted in human milk, caution should be exercised when LASTACAFT® is administered to a nursing woman.

8.4 Pediatric Use

Safety and effectiveness in pediatric patients below the age of 2 years have not been established.

8.5 Geriatric Use

No overall differences in safety or effectiveness were observed between elderly and younger subjects.

11 DESCRIPTION

LASTACAFT® is a sterile, topically administered H1 receptor antagonist containing alcaftadine for ophthalmic use.

Alcaftadine is a white to yellow powder with an empirical formula of C19H21N3O and a molecular weight of 307.39.

Contains: Active: alcaftadine 0.25% (2.5 mg/mL). Preservative: benzalkonium chloride 0.005%. Inactives: edetate disodium; sodium phosphate, monobasic; purified water; sodium chloride; sodium hydroxide and/or hydrochloric acid to adjust pH

Chemical Name: 6,11-dihydro-11-(1-methyl-4-piperidinylidene)-5H-imidazo[2,1-b] [3] benzazepine-3-carboxaldehyde

Structural Formula:

The drug product has a pH of approximately 7 and an osmolality of approximately 290 mOsm/kg.

12 CLINICAL PHARMACOLOGY

12.1 Mechanism of Action

Alcaftadine is an H1 histamine receptor antagonist and inhibitor of the release of histamine from mast cells. Decreased chemotaxis and inhibition of eosinophil activation has also been demonstrated.

12.3 Pharmacokinetics

Absorption

Following bilateral topical ocular administration of alcaftadine ophthalmic solution, 0.25%, the mean plasma Cmax of alcaftadine was approximately 60 pg/mL and the median Tmax occurred at 15 minutes. Plasma concentrations of alcaftadine were below the lower limit of quantification (10 pg/mL) by 3 hours after dosing. The mean Cmax of the active carboxylic acid metabolite was approximately 3 ng/mL and occurred at 1 hour after dosing. Plasma concentrations of the carboxylic acid metabolite were below the lower limit of quantification (100 pg/mL) by 12 hours after dosing. There was no indication of systemic accumulation or changes in plasma exposure of alcaftadine or the active metabolite following daily topical ocular administration.

Distribution

The protein binding of alcaftadine and the active metabolite are 39.2% and 62.7%, respectively.

Metabolism

The metabolism of alcaftadine is mediated by non-CYP450 cytosolic enzymes to the active carboxylic acid metabolite.

Excretion

The elimination half-life of the carboxylic acid metabolite is approximately 2 hours following topical ocular administration. Based on data following oral administration of alcaftadine, the carboxylic acid metabolite is primarily eliminated unchanged in the urine.

In vitro studies showed that neither alcaftadine nor the carboxylic acid metabolite substantially inhibited reactions catalyzed by major CYP450 enzymes.

13 NONCLINICAL TOXICOLOGY

13.1 Carcinogenesis, Mutagenesis, Impairment of Fertility

Alcaftadine was not mutagenic or genotoxic in the Ames test, the mouse lymphoma assay or the mouse micronucleus assay.

Alcaftadine was found to have no effect on fertility of male and female rats at oral doses up to 20 mg/kg/day (approximately 200 times the plasma exposure at the recommended human ocular dose).

14 CLINICAL STUDIES

Clinical efficacy was evaluated in conjunctival allergen challenge (CAC) studies. LASTACAFT® was more effective than its vehicle in preventing ocular itching in patients with allergic conjunctivitis induced by an ocular allergen challenge, both at 3 minutes post-dosing and at 16 hours post-dosing of LASTACAFT®.

The safety of LASTACAFT® was evaluated in a randomized clinical study of 909 subjects over a period of 6 weeks.

16 HOW SUPPLIED/STORAGE AND HANDLING

LASTACAFT® (alcaftadine ophthalmic solution) 0.25% is supplied in an opaque, white low-density polyethylene bottle with a white polypropylene cap.

3 mL fill in 5 mL bottle NDC 42254-288-03

STORAGE AND HANDLING

Storage: Store at 15-25°C (59-77°F).

17 PATIENT COUNSELING INFORMATION

17.1 Sterility of Dropper Tip

Patients should be advised to not touch dropper tip to any surface, as this may contaminate the contents.

17.2 Concomitant Use of Contact Lenses

Patients should be advised not to wear a contact lens if their eye is red. Patients should be advised that LASTACAFT® should not be used to treat contact lens-related irritation. Patients should also be advised to remove contact lenses prior to instillation of LASTACAFT®. The preservative in LASTACAFT®, benzalkonium chloride, may be absorbed by soft contact lenses. Lenses may be reinserted after 10 minutes following administration of LASTACAFT®.

17.3 Topical Ophthalmic Use Only

For topical ophthalmic administration only.

ALLERGAN
Manufactured for Allergan, Inc., Irvine, CA 92612, U.S.A.
© 2011 Allergan, Inc.
® marks owned by Allergan, Inc.
Made in the U.S.A.

72409US11C

Repackaged by:

REBEL DISTRIBUTORS CORP.

Thousand Oaks, CA 91320